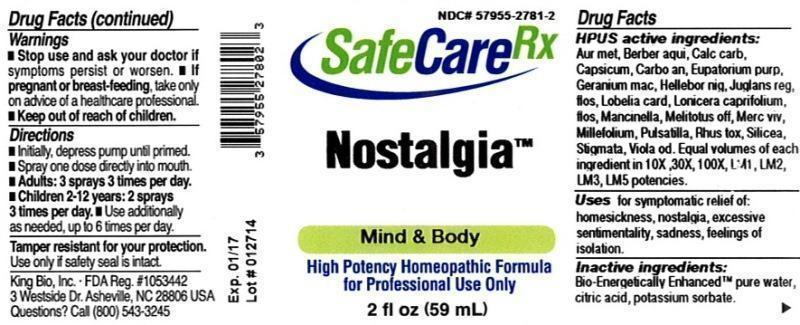 DRUG LABEL: Nostalgia
NDC: 57955-2781 | Form: LIQUID
Manufacturer: King Bio Inc.
Category: homeopathic | Type: HUMAN OTC DRUG LABEL
Date: 20140613

ACTIVE INGREDIENTS: GOLD 10 [hp_X]/59 mL; MAHONIA AQUIFOLIUM ROOT BARK 10 [hp_X]/59 mL; OYSTER SHELL CALCIUM CARBONATE, CRUDE 10 [hp_X]/59 mL; CAPSICUM 10 [hp_X]/59 mL; CARBO ANIMALIS 10 [hp_X]/59 mL; EUTROCHIUM PURPUREUM ROOT 10 [hp_X]/59 mL; GERANIUM MACULATUM ROOT 10 [hp_X]/59 mL; HELLEBORUS NIGER ROOT 10 [hp_X]/59 mL; JUGLANS REGIA FLOWERING TOP 10 [hp_X]/59 mL; LOBELIA CARDINALIS 10 [hp_X]/59 mL; LONICERA CAPRIFOLIUM FLOWERING TOP 10 [hp_X]/59 mL; HIPPOMANE MANCINELLA FRUITING LEAFY TWIG 10 [hp_X]/59 mL; MELILOTUS OFFICINALIS TOP 10 [hp_X]/59 mL; MERCURY 10 [hp_X]/59 mL; ACHILLEA MILLEFOLIUM 10 [hp_X]/59 mL; PULSATILLA VULGARIS 10 [hp_X]/59 mL; TOXICODENDRON PUBESCENS LEAF 10 [hp_X]/59 mL; SILICON DIOXIDE 10 [hp_X]/59 mL; CORN SILK 10 [hp_X]/59 mL; VIOLA ODORATA 10 [hp_X]/59 mL
INACTIVE INGREDIENTS: WATER; CITRIC ACID MONOHYDRATE; POTASSIUM SORBATE

Nostalgia™

ACTIVE INGREDIENT

Drug Facts__________________________________________________________________________________________________________

HPUS active ingredients: Aurum metallicum, Berberis aquifolium, Calcarea carbonica, Capsicum annuum, Carbo animalis, Eupatorium purpureum, Geranium maculatum, Helleborus niger, Juglans regia, flos, Lobelia cardinalis, Lonicera caprifolium, flos, Mancinella, Melilotus officinalis, Mercurius vivus, Millefolium, Pulsatilla, Rhus toxicodendron, Silicea, Stigmata maidis, Viola odorata. Equal volumes of each ingredient in 10X, 30X, 100X, LM1, LM2, LM3, LM5 potencies.

INDICATIONS AND USAGE

Uses for symptomatic relief of: homesickness, nostalgia, excessive sentimentality, sadness, feelings of isolation.

Inactive Ingredients:

Bio-Energetically Enhanced™ pure water, citric acid and potassium sorbate.

Warnings

- Stop use and ask your doctor if symptoms persist or worsen.
- If pregnant or breast-feeding, take only on advice of a healthcare professional.

- Keep out of reach of children.

Directions

- Initially, depress pump until primed.
- Spray one dose directly into mouth.
- Adults: 3 sprays 3 times per day.
- Children 2-12 years: 2 sprays 3 times per day.
- Use additionally as needed, up to 6 times per day.

OTHER SAFETY INFORMATION

Tamper resistant for your protection. Use only if safety seal is intact.

PURPOSE

Uses for symptomatic relief of:

- homesickness
- nostalgia
- excessive sentimentality
- sadness
- feelings of isolation